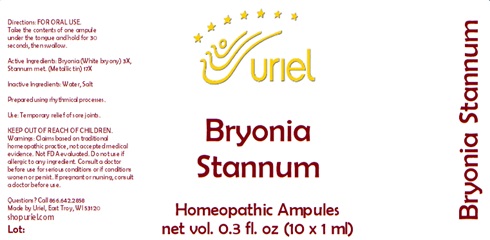 DRUG LABEL: Bryonia Stannum
NDC: 48951-2086 | Form: LIQUID
Manufacturer: Uriel Pharmacy Inc.
Category: homeopathic | Type: HUMAN OTC DRUG LABEL
Date: 20241217

ACTIVE INGREDIENTS: BRYONIA ALBA ROOT 3 [hp_X]/1 mL; TIN 17 [hp_X]/1 mL
INACTIVE INGREDIENTS: WATER; SODIUM CHLORIDE

Bryonia Stannum

INDICATIONS AND USAGE

Directions: FOR ORAL USE.

DOSAGE AND ADMINISTRATION

Take the contents of one ampule under the tongue and hold for 30 seconds, then swallow.

ACTIVE INGREDIENT

Active Ingredients: Bryonia (White bryony) 3X, Stannum met. (Metallic tin) 17X

Inactive Ingredients: Water, Salt

Prepared using rhythmical processes.

PURPOSE

Use: Temporary relief of sore joints.

KEEP OUT OF REACH OF CHILDREN.

WARNINGS

Warnings: Claims based on traditional homeopathic practice, not accepted medical evidence. Not FDA evaluated. Do not use if allergic to any ingredient. Consult a doctor before use for serious conditions or if conditions worsen or persist. If pregnant or nursing, consult a doctor before use.

Questions? Call 866.642.2858
Made by Uriel, East Troy, WI 53120
shopuriel.com Lot: